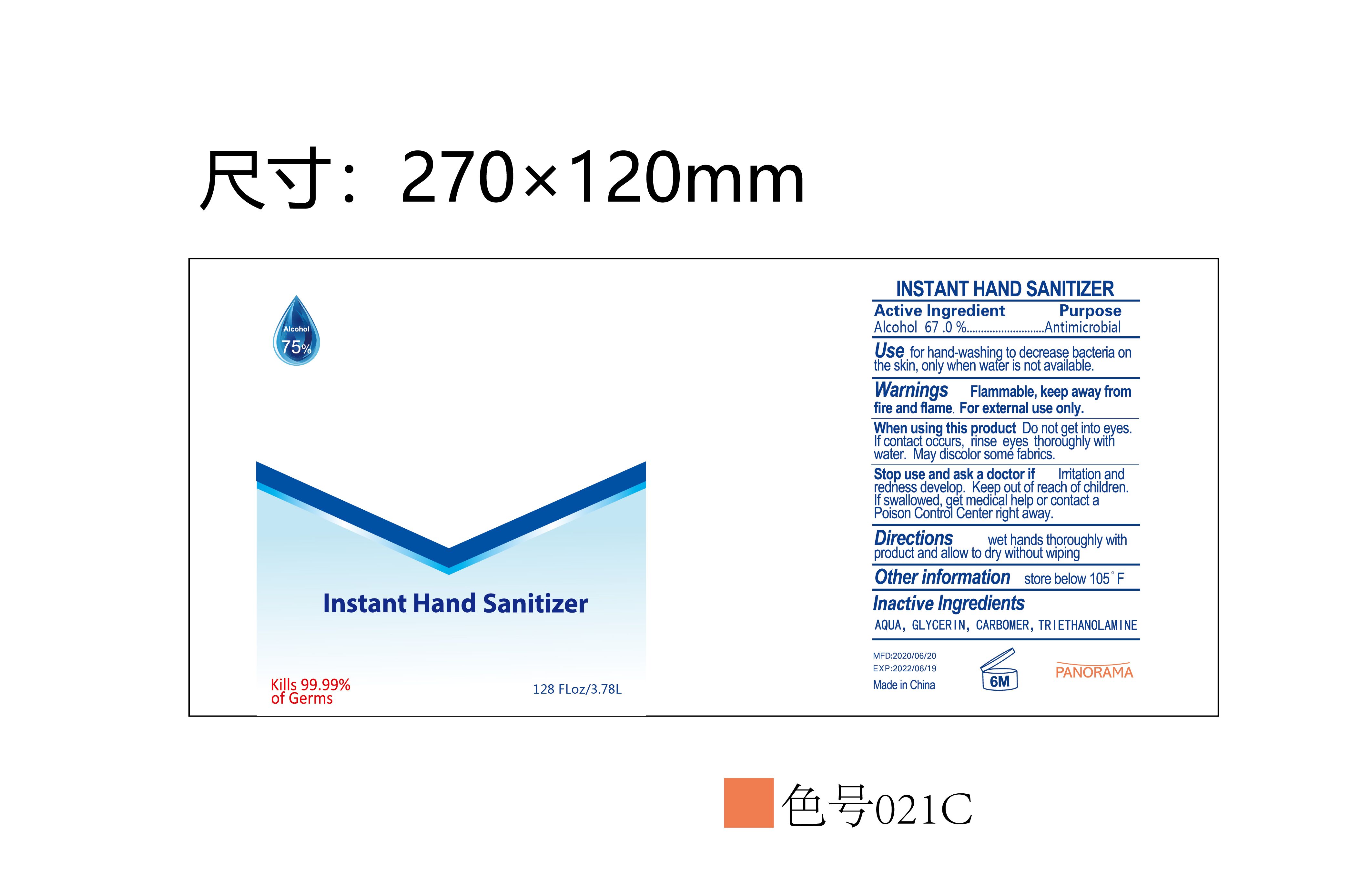 DRUG LABEL: INSTANT HAND SANITIZER
NDC: 79744-001 | Form: GEL
Manufacturer: Hangzhou KEON Biotech Co., Ltd.
Category: otc | Type: HUMAN OTC DRUG LABEL
Date: 20200819

ACTIVE INGREDIENTS: ALCOHOL 67 mL/100 mL
INACTIVE INGREDIENTS: GLYCERIN; CARBOMER HOMOPOLYMER, UNSPECIFIED TYPE; WATER; TROLAMINE

79744-001 INSTANT HAND SANITIZER

Active Ingredient(s)

Alcohol 67.0%

Purpose

Antimicrobial

Use

Use for hand-washing to decrease bacteria on the skin, only when wafer is not available.

Warnings

Warnings Flammable, keep away from fire and flame. For external use only.

Do not use

/

When using this product Do not get into eyes.
If contact occurs, rinse eyes thoroughly witti water. May discolor some fabrics.

Stop use and ask a doctor if Irritation and redness develop.

Keep out of reach of children.
If swallowed, get medical help or contact a Poison Control Center right away.

Directions

Directions wet hands thoroughly with product and allow to dry without wiping

Other information

Other information store below 1os °F

Inactive ingredients

AQUA, GLYCERIN, CARBOMER, TRIETHANOLAMINE